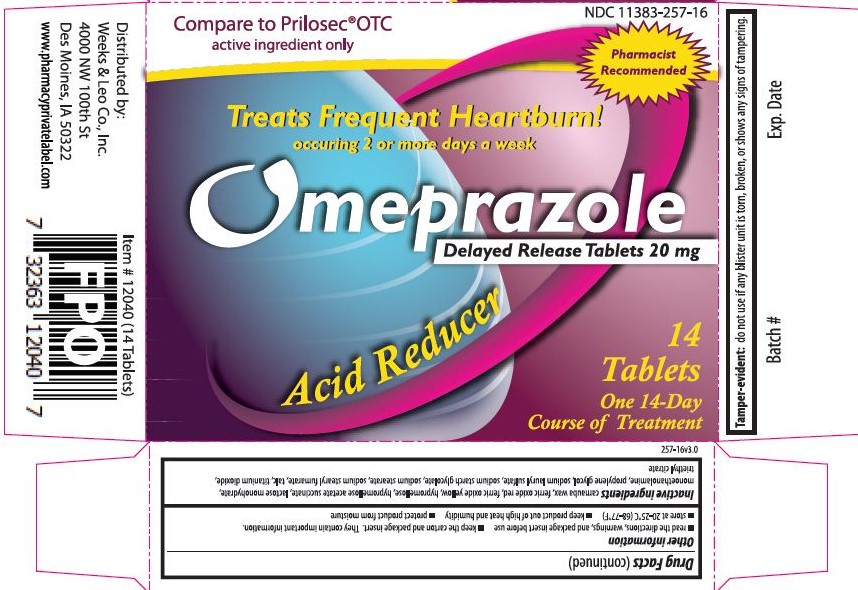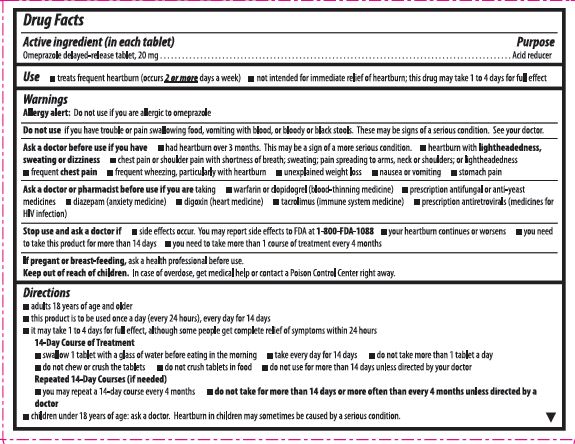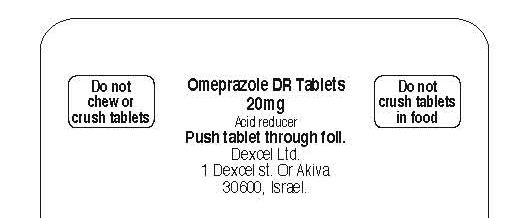 DRUG LABEL: Omeprazole
NDC: 11383-257 | Form: TABLET, DELAYED RELEASE
Manufacturer: Weeks & Leo Co., Inc.
Category: otc | Type: HUMAN OTC DRUG LABEL
Date: 20121010

ACTIVE INGREDIENTS: OMEPRAZOLE 20 mg/1 1
INACTIVE INGREDIENTS: CARNAUBA WAX; FERRIC OXIDE RED; FERRIC OXIDE YELLOW; HYPROMELLOSES; HYPROMELLOSE ACETATE SUCCINATE 12070923 (3 MM2/S); LACTOSE MONOHYDRATE; MONOETHANOLAMINE; PROPYLENE GLYCOL; SODIUM LAURYL SULFATE; SODIUM STARCH GLYCOLATE TYPE A POTATO; SODIUM STEARATE; SODIUM STEARYL FUMARATE; TALC; TITANIUM DIOXIDE; TRIETHYL CITRATE

Omeprazole Delayed Release Tablets, 20 mg

Active Ingredient (In each tablet)

Omeprazole delayed-release tablet, 20 mg

Purpose

Acid reducer

Use

- treats frequent heartburn (occurs 2 or more days a week)
- not intended for immediate relief of heartburn; this drug may take 1 to 4 days for full effect

Warnings

Allergy alert: Do not use if you are allergic to omeprazole

Do Not Use

if you have trouble or pain swallowing food, vomiting with blood, or bloody or black stools. These may be signs of a serious condition. See your doctor.

Ask a doctor before use if you have

had heartburn over 3 months. This may be a sign of a more serious condition.

- had heartburn over 3 months. This may be a sign of a more serious condition.
- heartburn with lightheadedness, sweating or dizziness
- chest pain or shoulder pain with shortness or breath; sweating; pain spreading to arms, neck or shoulders; or lightheadedness
- frequent chest pain
- frequent wheezing, particularly with heartburn
- unexplained weight loss
- nausea or vomiting
- stomach pain

Ask a doctor or pharmacist before use

if you are taking

- warfarin or clopidogrel (blood-thinning medicine)
- prescription antifungal or anti-yeast medicines
- diazepam (anxiety medicine)
- digoxin (heart medicine)
- tacrolimus (immune system medicine)
- preswcription antretroivirals (medicines for HIV infection)

Stop use and ask a doctor if

- side effects occur. You may report side effects to FDA at 1-800-FDA-1088
- your heartburn continues or worsens
- you need to take this product for more than 14 days
- you need to take more than 1 course of treatment every 4 months

If pregnant or breast-feeding,

ask a health professional before use.

Keep out of reach of children.

In case of overdose, get medical help or contact a Poison Control Center right away.

Directions

- adults 18 years of age and older
- this product is to be used once a day (every 24 hours), every day for 14 days
- it may take 1 to 4 days for full effect, although some people get complete relief of symptoms within 24 hours

14-Day Course of Treatment

- swallow 1 tablet with a glass of water before eating in the morning
- take every day for 14 days
- do not take more than 1 tablet a day
- do not chew or crush the tablets
- do not crush tablets in food
- do not use for more than 14 days unless directed by your doctor

Repeated 14-Day Courses (if needed)

- you may repeat a 14-day course every 4 months
- do not take for more than 14 days or more often than every 4 months unless directed by a doctor

- children under 18 years of age: ask a doctor. Heartburn in children may sometimes be caused by a serious condition.

Other information

- read the directions, warnings, and package insert before use
- keep the carton and package insert. They contain important information.
- store at 20-25°C (68-77°F)
- keep product out of high heat and humidity
- protect product from moisture

Inactive ingredients

carnauba wax, ferric oxide red, ferric oxide yellow, hypromellose, hypromellose acetate succinate, lactose monohydrate, monoethanolamine, propylene glycol, sodium lauryl sulfate, sodium starch glycolate, sodium stearate, sodium stearyl fumarate, talc, titanium dioxide, triethyl citrate

Tamper-evident:

do not use if any blister unit is torn, broken, or shows any signs of tampering.

Carton Label - 14 tablets

Treats Frequent Heartburn!
Occurring 2 or More Days a Week
Omeprazole
delayed release tablets 20 mg
acid reducer
14 TABLETS
One 14-day course of treatment

Comparare to Prilosec* OTC active ingredient only

Pharmacist Recommended
14 tablet box front

14 tablet box rear

Blister Label

Omeprazole DR Tablets
20 mg
Acid reducer
Push tablet through foil.
Dexcel Ltd.
1 Dexcel St. Or Akiva
30600, Israel
Do not chew or crush tablets
Do not crush tablets in food

Patient Package Insert

Omeprazole Delayed Release Tablets 20 mg
Acid Reducer
Please read all of this package insert before taking Omeprazole Delayed Release Tablets 20 mg. Save this to read, as you need.
How Omeperazole Delayed Release Tablets 20 mg Work For Your Frequent Heartburn
Omeprazole Delayed Release Tablets 20 mg work differently from other heartburn products, such as antacids and other acid reducers. Omeprazole Delayed Release Tablets 20 mg stop acid production at the source - the acid pump that produces stomach acid. Omeprazole Delayed Release Tablets 20 mg are to be used once a day (every 24 hours), every day for 14 days.
What to Expect When Using Omeprazole Delayed Release Tablets 20 mg
Omeprazole Delayed Release Tablets 20 mg are a different type of medicine from antacids and other acid reducers. Omeprazole Delayed Release Tablets 20 mg may take 1 to 4 days for full effect, although some people get complete relief of symptoms within 24 hours. Make sure you take the entire 14 days of dosing to treat your frequent heartburn.
Safety Record
For years, doctors have prescribed omeprazole to treat acid-related conditions in millions of people safely.
Who Should Take Omeprazole Delayed Release Tablets 20 mg
This product is for adults (18 years and older) with frequent heartburn - when you have heartburn 2 or more days a week.

- Omeprazole Delayed Release Tablets 20 mg are not intended for those who have heartburn infrequently, one episode of heartburn a week or less, or for those who want immediate relief or heartburn.

How to Take Omeprazole Delayed Release Tablets 20 mg
14-Day Course of Treatment

- Swallow 1 tablet with a glass of water before eating in the morning.
- Take every day for 14 days.
- Do not take more than 1 tablet a day
- Do not chew or crush the tablets.
- Do not crush tablets in food.
- Do not use for more than 14 days unless directed by your doctor.

It is important not to chew or crush these tablets, or crush the tablets in food. This decreases how well Omeprazole Delayed Release Tablets 20 mg work.
When to Take Omeprazole Delayed Release Tablets 20 mg Again
You may repeat a 14-day course of therapy every 4 months.
When to Talk to Your Doctor
Do not take for more than 14 days or more often than every 4 months unless directed by a doctor.
Warnings and When to Ask Your Doctor
Allergy alert: Do not use if you are allergic to omeprazole
Do not use if you have trouble or pain swallowing food, vomiting with blood, or bloody or black stools. These may be signs of a serious condition. See your doctor.
Ask a doctor before use if you have

- had heartburn over 3 months. This may be a sign of a more serious condition
- heartburn with lightheadedness, sweating or dizziness
- chest pain or shoulder pain with shortness of breath; sweating; pain spreading to arms, neck or shoulders; or lightheadedness
- frequent chest pain
- frequent wheezing, particularly with heartburn
- unexplained weight loss
- nausea or vomiting
- stomach pain

Ask a doctor or pharmacist before use if you are taking

- clopidogrel bisulfate (anti-blood clotting medicine)
- warfarin (blood-thinning medicine)
- prescription antifungal or anti-yeast medicines
- diazepam (anxiety medicine)
- digoxin (heart medicine)
- tacrolimus (immune system medicine)
- atazanavir (medicine for HIV infection)

Stop use and ask a doctor if

- your heartburn continues or worsens
- you need to take this product for more than 14 days
- you need to take more than 1 course of treatment every 4 months

If pregnant or breast-feeding,
ask a health professional before use.
Keep out of reach of children.
In case of overdose, get medical help or contact a Poison Control Center right away. (1-800-222-1222)
Tips for Managing Heartburn

- Do not lie flat or bend over soon after eating.
- Do not eat late at night or just before bedtime.
- Certain foods or drinks are more likely to cause heartburn, such as rich, spicy, fatty and fried foods, chocolate, caffeine, alcohol and even some fruits and vegetables.
- Eat slowly and do not eat big meals.
- If you are overweight, lose weight.
- If you smoke, quit smoking.
- Raise the head of your bed.
- Wear loose-fitting clothing around your stomach.

How are Omeprazole Delayed Release Tablets 20 mg Sold
Omeprazole Delayed Release Tablets 20 mg are available in 14 tablet, 28 tablet and 42 tablet sizes. These sizes contain one, two and three 14-day courses of treatment, respectively. Do not use for more than 14 days in a row unless directed by your doctor. For the 28 count (two 14-day courses) and the 42 count (three 14-day courses), you may repeat a 14-day course every 4 months.
For Questions or Comments About Omeprazole Delayed Release Tablets 20 mg
Call 1-800-719-9260
Made in Israel
Manufactured by:
DEXCEL® LTD.
Southern Industrial Zone
Or Akiva 30600, Israel